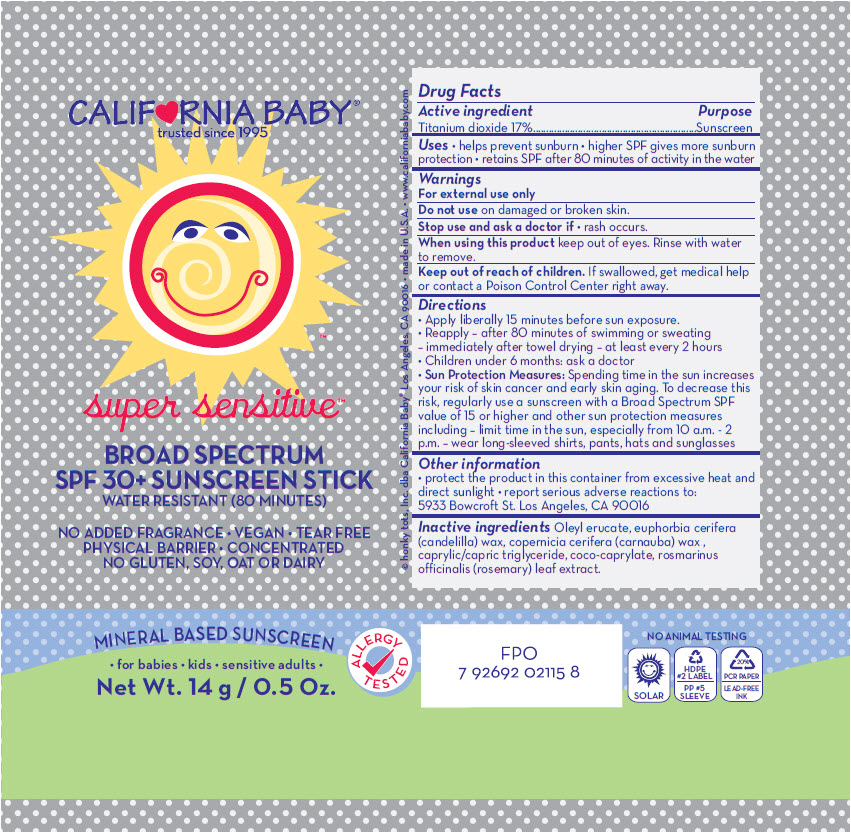 DRUG LABEL: SPF30 SUPER SENSITIVE SUNSCREEN
NDC: 52915-070 | Form: STICK
Manufacturer: ORGANIC & SUSTAINABLE BEAUTY
Category: otc | Type: HUMAN OTC DRUG LABEL
Date: 20241108

ACTIVE INGREDIENTS: TITANIUM DIOXIDE 170 mg/1 g
INACTIVE INGREDIENTS: oleyl erucate; candelilla wax; carnauba wax; medium-chain triglycerides; coco-caprylate; rosemary

SPF30 SUPER SENSITIVE™ SUNSCREEN STICK

Drug Facts

Active ingredient

Titanium dioxide 17%

Purpose

Sunscreen

Uses

- helps prevent sunburn
- higher SPF gives more sunburn protection
- retains SPF after 80 minutes of activity in the water

Warnings

For external use only

Do not use on damaged or broken skin.

Stop use and ask a doctor if

- rash occurs.

When using this product keep out of eyes. Rinse with water to remove.

Keep out of reach of children. If swallowed, get medical help or contact a Poison Control Center right away.

Directions

- Apply liberally 15 minutes before sun exposure.
- Reapply
  - after 80 minutes of swimming or sweating
  - immediately after towel drying
  - at least every 2 hours
- Children under 6 months: ask a doctor
- Sun Protection Measures: Spending time in the sun increases your risk of skin cancer and early skin aging. To decrease this risk, regularly use a sunscreen with a Broad Spectrum SPF value of 15 or higher and other sun protection measures including
  - limit time in the sun, especially from 10 a.m. - 2 p.m.
  - wear long-sleeved shirts, pants, hats and sunglasses

Other information

- protect the product in this container from excessive heat and direct sunlight
- report serious adverse reactions to: 5933 Bowcroft St. Los Angeles, CA 90016

Inactive ingredients

Oleyl erucate, euphorbia cerifera (candelilla) wax, copernicia cerifera (carnauba) wax , caprylic/capric triglyceride, coco-caprylate, rosmarinus officinalis (rosemary) leaf extract.

PRINCIPAL DISPLAY PANEL - 14 g Container Label

CALIF♥RNIA BABY®
trusted since 1995

super sensitive™

BROAD SPECTRUM
SPF 30+ SUNSCREEN STICK
WATER RESISTANT (80 MINUTES)

NO ADDED FRAGRANCE • VEGAN • TEAR FREE
PHYSICAL BARRIER • CONCENTRATED
NO GLUTEN, SOY, OAT OR DAIRY

MINERAL BASED SUNSCREEN
• for babies • kids • sensitive adults •

Net Wt. 14 g / 0.5 Oz.

ALLERGY
TESTED